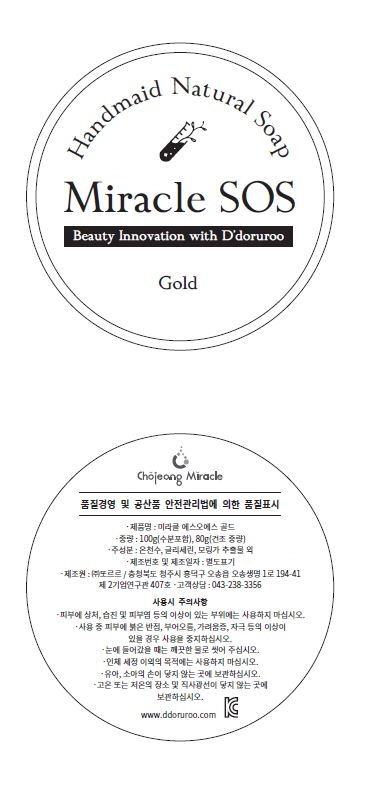 DRUG LABEL: MIRACLE SOS GOLD
NDC: 71484-0002 | Form: SOAP
Manufacturer: Ddoruroo Co., Ltd.
Category: otc | Type: HUMAN OTC DRUG LABEL
Date: 20170619

ACTIVE INGREDIENTS: MORINGA OLEIFERA LEAF 33.8 g/100 g
INACTIVE INGREDIENTS: GLYCERIN

Drug Facts

ACTIVE INGREDIENT

Moringa Oleifera Leaf Extract, Bamboo Charcoal Powder

INACTIVE INGREDIENT

Stearic Acid, Myristic Acid, Lauric Acid, etc.

PURPOSE

SKIN PROTECTANT

KEEP OUT OF REACH OF THE CHILDREN

INDICATIONS AND USAGE

After make soap bubbles with lukewarm water and then wash the face sofly while massaging the entire face.

WARNINGS

1. Do not use in the following cases(Eczema and scalp wounds)
2.Side Effects
1)Due to the use of this druf if rash, irritation, itching and symptopms of hypersnesitivity occur dicontinue use and consult your phamacisr or doctor
3.General Precautions
1)If in contact with the eyes, wash out thoroughty with water If the symptoms are servere, seek medical advice immediately
2)This product is for exeternal use only. Do not use for internal use
4.Storage and handling precautions
1)If possible, avoid direct sunlight and store in cool and area of low humidity
2)In order to maintain the quality of the product and avoid misuse
3)Avoid placing the product near fire and store out in reach of children

DOSAGE AND ADMINISTRATION

for external use only